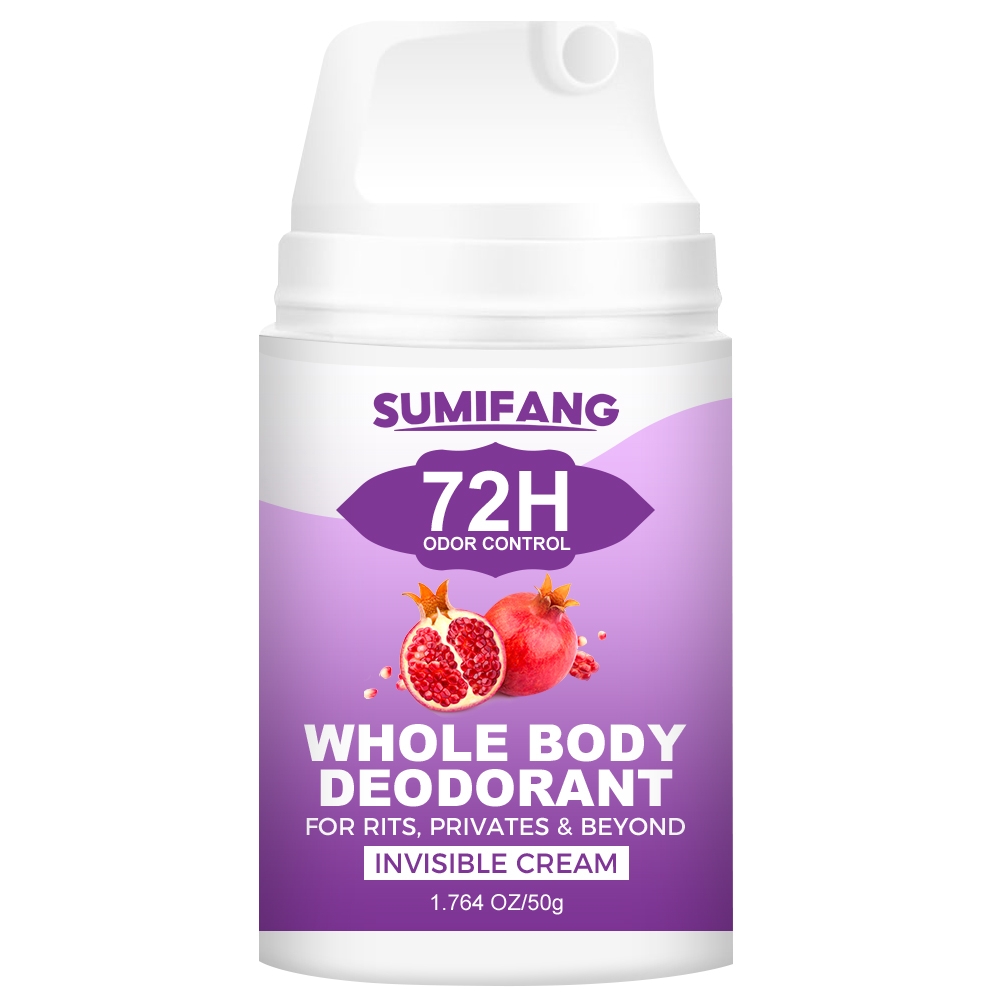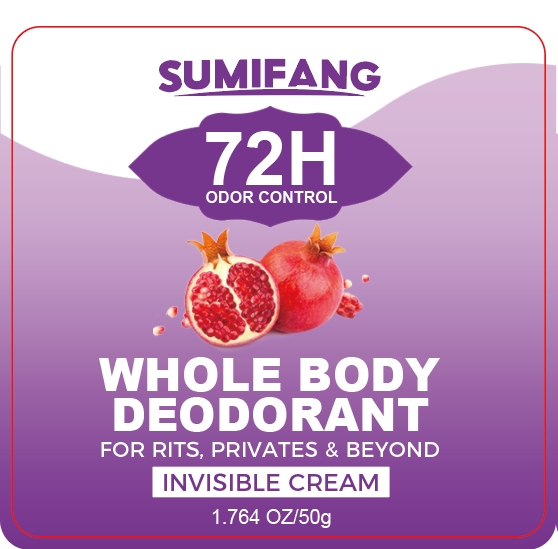 DRUG LABEL: DEODORANT WHOLEBODY
NDC: 84025-153 | Form: LIQUID
Manufacturer: Guangzhou Yanxi Biotechnology Co.. Ltd
Category: otc | Type: HUMAN OTC DRUG LABEL
Date: 20240817

ACTIVE INGREDIENTS: GLYCERIN 3 mg/50 g; HYALURONIC ACID 5 mg/50 g
INACTIVE INGREDIENTS: WATER

DOSAGE AND ADMINISTRATION

Used to moisturize the skin and control body odor

WARNINGS

Keep out of children

INACTIVE INGREDIENT

Aqua

INDICATIONS AND USAGE

for daily skin care

Keep out of children

PURPOSE

Effectively moisturizes the skin and removes skin odor